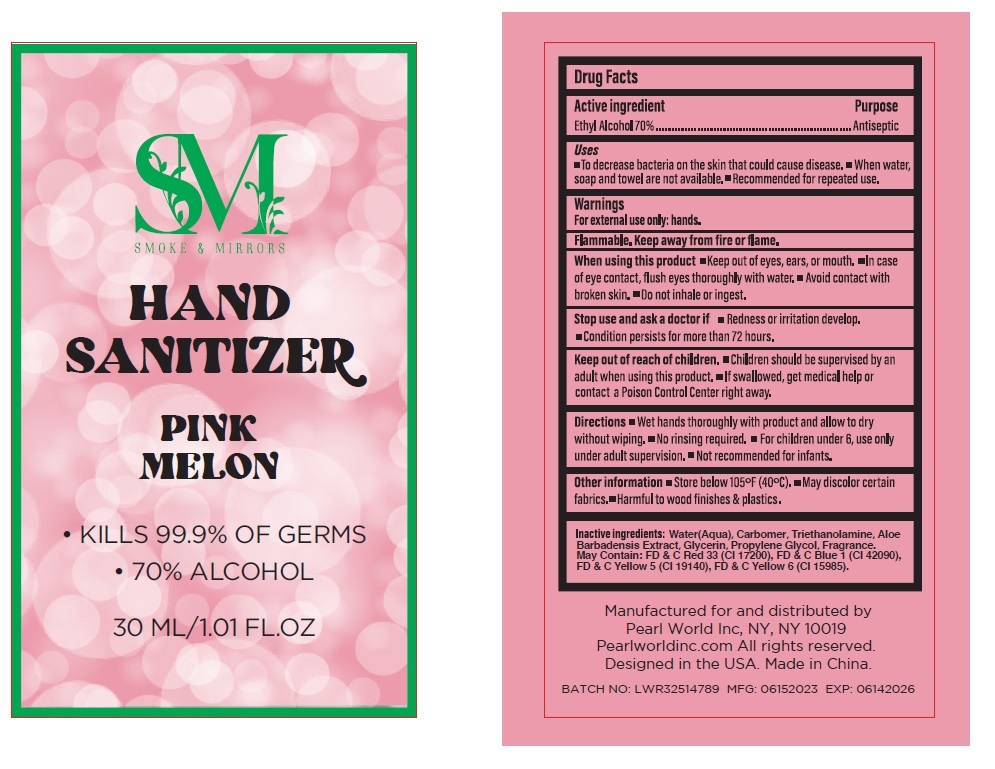 DRUG LABEL: Smoke and Mirrors Hand Sanitizer Pink Melon
NDC: 69933-895 | Form: GEL
Manufacturer: Pearl World Inc.
Category: otc | Type: HUMAN OTC DRUG LABEL
Date: 20230613

ACTIVE INGREDIENTS: ALCOHOL 70 mL/100 mL
INACTIVE INGREDIENTS: WATER; CARBOMER HOMOPOLYMER, UNSPECIFIED TYPE; TROLAMINE; ALOE VERA LEAF; GLYCERIN; PROPYLENE GLYCOL

SMOKE & MIRRORS HAND SANITIZER PINK MELON

Active ingredient

Ethyl Alcohol 70%

Purpose

Antiseptic

Uses

• To decrease bacteria on the skin that could cause disease. • When water, soap and towel are not available. • Recommended for repeated use.

Warnings

For external use only: hands.

Flammable. Keep away from fire or flame.

When using this product • Keep out of eyes, ears, or mouth. • In case of eye contact, flush eyes thoroughly with water. • Avoid contact with broken skin. • Do not inhale or ingest.

Stop use and ask a doctor if • Redness or irritation develop. • Condition persists for more than 72 hours.

Keep out of reach of children. • Children should be supervised by an adult when using this product • If swallowed, get medical help or contact a Poison Control Center right away.

Directions

• Wet hands thoroughly with product and allow to dry without wiping. • No rinsing required. • For children under 6, use only under adult supervision. • Not recommended for infants.

Other information

• Store below 105°F (40°C). • May discolor certain fabrics. • Harmful to wood finishes & plastics.

Inactive ingredients:

Water (Aqua), Carbomer, Triethanolamine, Aloe Barbadensis Extract, Glycerin, Propylene Glycol, Fragrance.
May Contain: FD & C Red 33 (CI 17200), FD & C Blue 1 (CI 42090), FD & C Yellow 5 (CI 19140), FD & C Yellow 6 (CI 15985).

- KILLS 99.9% OF GERMS

- 70% ALCOHOL

Manufactured for and distributed by

Pearl World Inc, NY, NY 10019

Pearlworldinc.com All rights reserved.

Designed in the USA. Made in China.